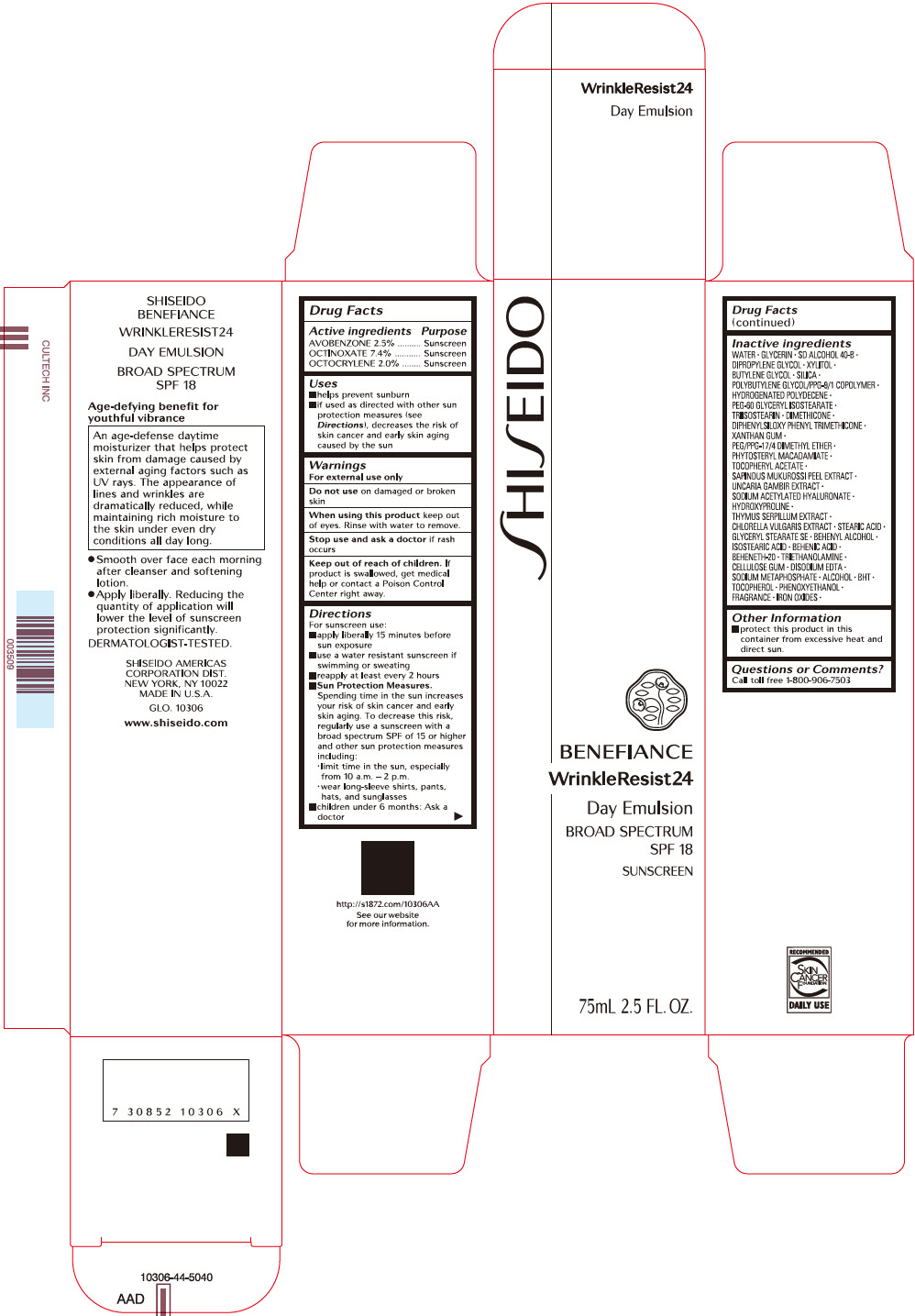 DRUG LABEL: SHISEIDO BENEFIANCE WRINKLERESIST24 DAY
NDC: 58411-628 | Form: EMULSION
Manufacturer: SHISEIDO AMERICAS CORPORATION
Category: otc | Type: HUMAN OTC DRUG LABEL
Date: 20260106

ACTIVE INGREDIENTS: AVOBENZONE 1.94 g/75 mL; OCTINOXATE 5.83 g/75 mL; OCTOCRYLENE 1.55 g/75 mL
INACTIVE INGREDIENTS: WATER; GLYCERIN; DIPROPYLENE GLYCOL; XYLITOL; BUTYLENE GLYCOL; SILICON DIOXIDE; HYDROGENATED POLYDECENE TYPE I; PEG-60 GLYCERYL ISOSTEARATE; TRIISOSTEARIN; DIMETHICONE; DIPHENYLSILOXY PHENYL TRIMETHICONE; XANTHAN GUM; PEG/PPG-17/4 DIMETHYL ETHER; PHYTOSTERYL MACADAMIATE; .ALPHA.-TOCOPHEROL ACETATE, DL-; SAPINDUS MUKOROSSI FRUIT RIND; UNCARIA GAMBIR WHOLE; SODIUM ACETYLATED HYALURONATE; HYDROXYPROLINE; CHLORELLA VULGARIS; STEARIC ACID; GLYCERYL MONOSTEARATE; DOCOSANOL; ISOSTEARIC ACID; BEHENIC ACID; BEHENETH-20; TROLAMINE; CARBOXYMETHYLCELLULOSE SODIUM, UNSPECIFIED; EDETATE DISODIUM; SODIUM POLYMETAPHOSPHATE; ALCOHOL; BUTYLATED HYDROXYTOLUENE; .ALPHA.-TOCOPHEROL; PHENOXYETHANOL; FERRIC OXIDE RED; FERRIC OXIDE YELLOW; FERROSOFERRIC OXIDE

SHISEIDO BENEFIANCE WRINKLERESIST24 DAY EMULSION

Drug Facts

ACTIVE INGREDIENT

Active ingredients | Purpose
AVOBENZON 2.5 % | Sunscreen
OCTINOXATE 7.4 % | Sunscreen
OCTOCRYLENE 2.0 % | Sunscreen

Uses

- helps prevent sunburn
- if used as directed with other sun protection measures (see Directions), decreases the risk of skin cancer and early skin aging caused by the sun

Warnings

For external use only

Do not use on damaged or broken skin

WHEN USING

When using this productkeep out of eyes. Rinse with water to remove.

Stop use and ask a doctorif rash occurs.

Keep out of reach of children.If product is swallowed, get medical help or contact a Poison Control Center right away.

Directions

For sunscreen use:

- apply liberally 15 minutes before sun exposure
- use a water resistant sunscreen if swimming or sweating
- reapply at least every two hours
- Sun Protection Measures.
  Spending time in the sun increases your risk of skin cancer and early skin aging. To decrease this risk, regularly use a sunscreen with a broad spectrum SPF of 15 or higher and other sun protection measures including:
  - limit time in the sun, especially from 10 a.m. – 2 p.m.
  - wear long-sleeve shirts, pants, hats, and sunglasses
  - children under 6 months: Ask a doctor

Inactive Ingredients

WATER•GLYCERIN•SD ALCOHOL 40-B•DIPROPYLENE GLYCOL•XYLITOL•BUTYLENE GLYCOL•SILICA•POLYBUTYLENE GLYCOL/PPG-9/1 COPOLYMER•HYDROGENATED POLYDECENE•PEG-60 GLYCERYL ISOSTEARATE•TRIISOSTEARIN•DIMETHICONE•DIPHENYLSILOXY PHENYL TRIMETHICONE•XANTHAN GUM•PEG/PPG-17/4 DIMETHYL ETHER•PHYTOSTERYL MACADAMIATE•TOCOPHERYL ACETATE•SAPINDUS MUKUROSSI PEEL EXTRACT•UNCARIA GAMBIR EXTRACT•SODIUM ACETYLATED HYALURONATE•HYDROXYPROLINE•THYMUS SERPILLUM EXTRACT•CHLORELLA VULGARIS EXTRACT•STEARIC ACID•GLYCERYL STEARATE SE•BEHENYL ALCOHOL•ISOSTEARIC ACID•BEHENIC ACID•BEHENETH-20•TRIETHANOLAMINE•CELLULOSE GUM•DISODIUM EDTA•SODIUM METAPHOSPHATE•ALCOHOL•BHT•TOCOPHEROL•PHENOXYETHANOL•FRAGRANCE•IRON OXIDES•

Other information

Protect this product in this container from excessive heat and direct sun.

Questions or comments?

Call toll free 1-800-906-7503

PRINCIPAL DISPLAY PANEL - 75 mL Bottle Carton

SHISEIDO

BENEFIANCE

WrinkleResist24

Day Emulsion

BROAD SPECTRUM
SPF 18
SUNSCREEN

75mL 2.5 FL. OZ.